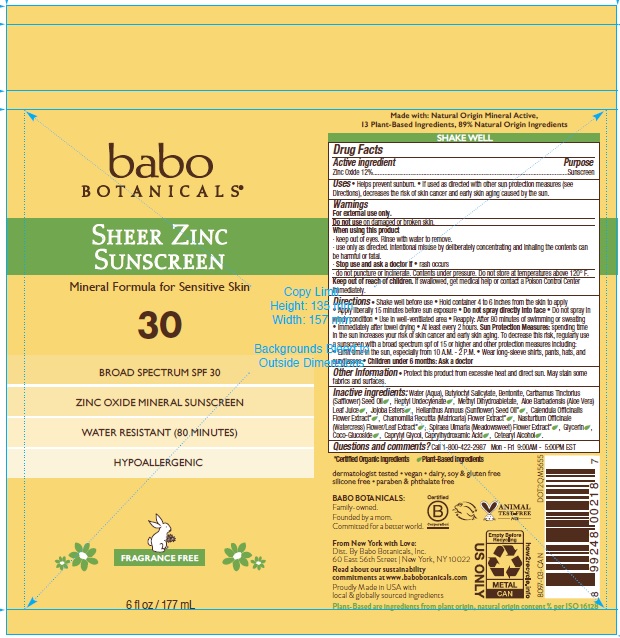 DRUG LABEL: Babo SPF 30 Sheer Zinc Sunscreen
NDC: 79265-8097 | Form: SPRAY
Manufacturer: Babo Botanicals, Inc.
Category: otc | Type: HUMAN OTC DRUG LABEL
Date: 20241212

ACTIVE INGREDIENTS: ZINC OXIDE 12.222 g/100 mL
INACTIVE INGREDIENTS: CALENDULA OFFICINALIS FLOWER; CETOSTEARYL ALCOHOL; CHAMOMILE; SUNFLOWER OIL; BUTYLOCTYL SALICYLATE; METHYL DIHYDROABIETATE; FILIPENDULA ULMARIA FLOWER; BENTONITE; CAPRYLHYDROXAMIC ACID; CAPRYLYL GLYCOL; WATER; SAFFLOWER OIL; HYDROGENATED JOJOBA OIL, RANDOMIZED; NASTURTIUM OFFICINALE FLOWERING TOP; COCO GLUCOSIDE; HEPTYL UNDECYLENATE; ALOE VERA LEAF; GLYCERIN

8097 Babo SPF 30 Sheer Zinc Sunscreen

Active Ingredient(s)

Zinc Oxide 12%

Purpose

Sunscreen

Uses

• Helps prevent sunburn. • If used as directed with other sun protection measures (see Directions), decreases the risk of skin cancer and early skin aging caused by the sun.

Warnings

For external use only.

Do not use

on damaged or broken skin.

When using this product

- keep out of eyes. Rinse with water to remove. Rinse with water to remove.
- use only as directed. Intentional misuse by deliberately concentrating and inhaling the contents can be harmful or fatal.

Stop use and ask a doctor if

- rash occurs.
- do not puncture or incinerate. Contents under pressure. Do not store at temperatures above 120F.

Keep out of reach of children.

If swallowed, get medical help or contact a Poison Control Center immediately.

Directions

Shake well before use • Hold container 4 to 6 inches from the skin to apply • Apply liberally 15 minutes before sun exposure • Do not spray directly into face • Do not spray in windy condition • Use in well-ventilated area • Reapply: After 80 minutes of swimming or sweating • Immediately after towel drying • At least every 2 hours. Sun Protection Measures: spending time in the sun increases your risk of skin cancer and early skin aging. To decrease this risk, regularly use a sunscreen with a broad spectrum spf of 15 or higher and other protection measures including: • Limit time in the sun, especially from 10 A.M. - 2 P.M. • Wear long-sleeve shirts, pants, hats, and sunglasses • Children under 6 months: Ask a doctor

Other information

- Protect this product from excessive heat and direct sun. May stain some fabrics and surfaces.

Inactive ingredients

Water (Aqua), Butyloctyl Salicylate, Bentonite, Carthamus Tinctorius (Safflower) Seed Oil, Heptyl Undecylenate, Methyl Dihydroabietate, Aloe Barbadensis (Aloe Vera) Leaf Juice, Jojoba Esters, Helianthus Annuus (Sunflower) Seed Oil*, Calendula Officinalis Flower Extract*, Chamomilla Recutita (Matricaria) Flower Extract*, Nasturtium Officinale (Watercress) Flower/Leaf Extract*, Spiraea Ulmaria (Meadowsweet) Flower Extract*, Glycerin, Coco-Glucoside, Caprylyl Glycol, Caprylhydroxamic Acid, Cetearyl Alcohol.

Questions and comments?

Call 1-800-422-2987 Mon - Fri 9:00AM - 5:00PM EST